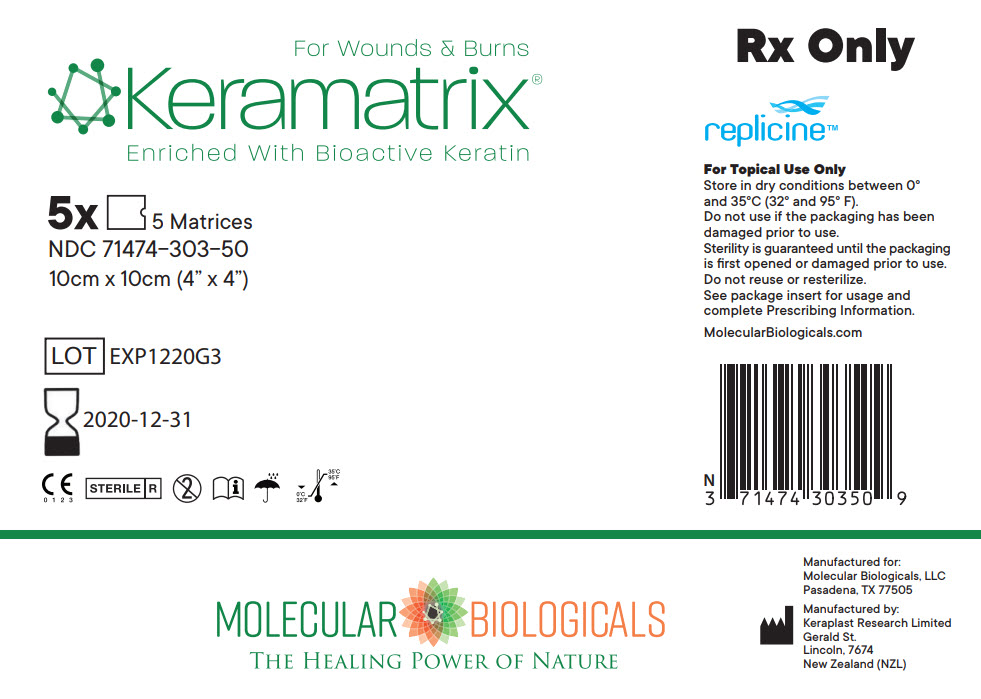 DRUG LABEL: keramatrix
NDC: 71474-303 | Form: NOT APPLICABLE
Manufacturer: Molecular Biologicals, LLC
Category: other | Type: PRESCRIPTION MEDICAL DEVICE LABEL
Date: 20190318

ACTIVE INGREDIENTS: AMINO ACIDS, HAIR KERATIN 100 mg/1 1

keramatrix®

Wound Matrix

Rx Prescription Only
Single Use

STERILE | R

C E
0 1 2 3

CAUTION

Federal (U.S.A.) law restricts this device to sale by or on the order of a physician(or properly licensed Healthcare practitioner).

INDICATIONS FOR USE

Acute surgical wounds, donor sites/grafts, podiatric wounds, wound dehiscence, diabetic ulcers, traumatic wounds, first & second degree Burns, chronic vascular ulcers, venous ulcers, Pressure ulcers, partial & full thickness wounds.

SUGGESTED DIRECTIONS FOR USE

NOTE: ALWAYS HANDLE USING ASEPTIC TECHNIQUE

WOUND BED PREPARATION & APPLICATION | MATRIX CHANGES AND REAPPLICATIONS
1. Prepare wound area using standard debridement methods to ensure the wound is free of debris and devitalized tissue. The wound may be surgically debrided to ensure the wound edges contain viable tissue. 2. Cut the dry keramatrix® sheet into a piece slightly larger than the outline of the wound area. If the wound is larger than a single sheet then multiple sheets may be used,overlapping edges as necessary. 3. For a wound with a low-level of exudate hydrate the matrix by soaking it in sterile saline solution for 2 minutes prior to application. 4. Place the edge of the sheet in contact with intact tissue and smooth the matrix so that it contacts the underlying wound bed. If multiple matrices are used, overlap adjoining sheets to provide coverage of the entire wound. Secure with the preferred method of fixation[steri-strips, sutures, staples, clips}. 5. After application use an appropriate, non-adherent, occlusive secondary dressing to maintain a moist environment. Ensure the matrix is well restrained. | 6. Change keramatrix® sheet as necessary every 4 to 5 days days or as determined by the healthcare provider. Do not remove existing gel or matrix areas. The matrix will caramelize into a gel and have a off white light brown color. 7. Once cleansed with Sterile Saline solution keramatrix may be reapplied. Ensure that there are no bleeding areas and that the wound edges are clean. 8. For a wound with a medium to high level of exudate, place the edge of the sheet in contact with intact tissue and smooth the so that it contacts the underlying wound bed. Small openings can be cut into the sheet prior to application to allow adequate drainage and ensure tissue matrix contact with the wound bed. 9. Carefully document healing progression using customary healing parameters. Proceed with reapplication of appropriate non-adherent occlusive secondary dressing and maintain a moist environment. 10. If infection, excessive redness, blistering or allergic reaction occurs the matrix material should be removed.

CONTRAINDICATIONS

Any known sensitivity to keratin.

PRECAUTIONS

Do not reuse or re-sterilize. Do not use if package is open or unsealed. Use prior to expiration date.

STORAGE

Do not use if pouch has been opened or damaged. Should be stored at a clean, dry location at room temperature.

HOW SUPPLIED

keramatrix is supplied in a clear pouch with labelled unit cartons.

keramatrix 5cm ×5cm Individual unit | 71474-303-05
keramatrix 5cm × 5cm Box of 5 units | 71474-303-55
keramatrix 5cm × 5cm Box of 10 units | 71474-303-51
keramatrix 10cm × 10cm Individual unit | 71474-303-01
keramatrix 10cm × 10cm Box of 5 units | 71474-303-50
keramatrix 10cm × 10cm Box of 10 units | 71474-303-10

Manufactured for:
Molecular Biologicals, LLC
Pasadena, TX 77505 | 1-844-793-9933
By Keraplast Research Limited
Gerald St, Lincoln 7674 NZ

PRINCIPAL DISPLAY PANEL - 5 Matrix Package Box Label

For Wounds & Burns
Keramatrix®
Enriched With Bioactive Keratin

5x 5 Matrices
NDC 71474-303-50
10cm x 10cm (4" x 4")

LOT EXP1220G3

2020-12-31

CE
0123
STERILE R

Rx Only

replicine™

For Topical Use Only
Store in dry conditions between 0°
and 35°C (32° and 95° F).
Do not use if the packaging has been
damaged prior to use.
Sterility is guaranteed until the packaging
is first opened or damaged prior to use.
Do not reuse or resterilize.
See package insert for usage and
complete Prescribing Information.

MolecularBiologicals.com

MOLECULAR BIOLOGICALS

THE HEALING POWER OF NATURE

Manufactured for:
Molecular Biologicals, LLC
Pasadena, TX 77505

Manufactured by:
Keraplast Research Limited
Gerald St.
Lincoln, 7674
New Zealand (NZL)